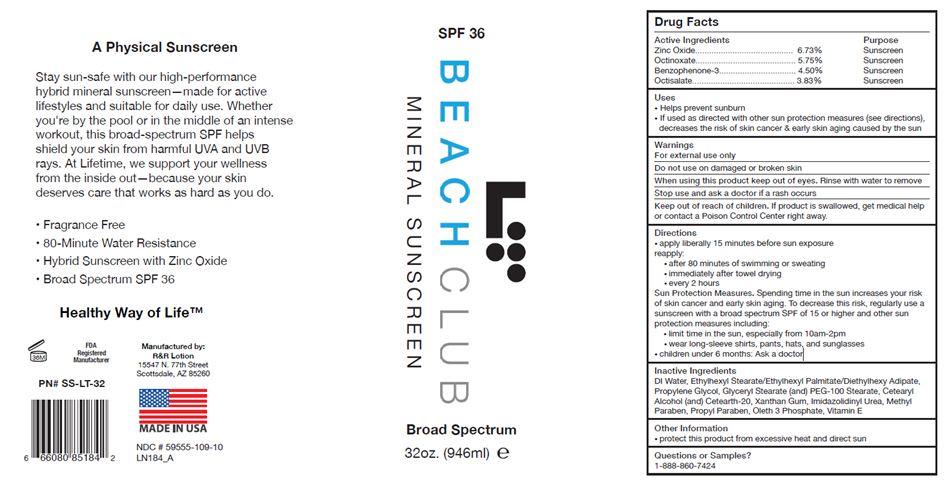 DRUG LABEL: Beach Club Mineral Sunscreen
NDC: 59555-109 | Form: LOTION
Manufacturer: R & R Lotion, Inc
Category: otc | Type: HUMAN OTC DRUG LABEL
Date: 20250912

ACTIVE INGREDIENTS: Zinc Oxide 67.3 mg/1 mL; Octinoxate 57.5 mg/1 mL; OXYBENZONE 45 mg/1 mL; Octisalate 38.3 mg/1 mL
INACTIVE INGREDIENTS: WATER; Ethylhexyl Stearate; Ethylhexyl Palmitate; Diethylhexyl Adipate; Propylene Glycol; GLYCERYL MONOSTEARATE; PEG-100 Stearate; CETOSTEARYL ALCOHOL; POLYOXYL 20 CETOSTEARYL ETHER; Xanthan Gum; IMIDUREA; METHYLPARABEN; PROPYLPARABEN; Oleth-3 Phosphate; .ALPHA.-TOCOPHEROL ACETATE

Beach Club Mineral Sunscreen

Drug Facts

ACTIVE INGREDIENT

Active Ingredients |  |  | Purpose
Zinc Oxide | 6.73% |  | Sunscreen
Octinoxate | 5.75% |  | Sunscreen
Benzophenone-3 | 4.50% |  | Sunscreen
Octisalate | 3.83% |  | Sunscreen

Uses

- Helps prevent sunburn
- If used as directed with other sun protection measures (see directions), decreases the risk of skin cancer & early skin aging caused by the sun

Warnings

For external use only

Do not use on damaged or broken skin

When using this product keep out of eyes. Rinse with water to remove

Stop use and ask a doctor if a rash occurs

Keep out of reach of children. If product is swallowed, get medical help or contact a Poison Control Center right away.

Directions

- apply liberally 15 minutes before sun exposure reapply:
  - after 80 minutes of swimming or sweating
  - immediately after towel drying
  - every 2 hours
Sun Protection Measures. Spending time in the sun increases your risk of skin cancer and early skin aging. To decrease this risk, regularly use a sunscreen with a broad spectrum SPF of 15 or higher and other sun protection measures including:
  - limit time in the sun, especially from 10am-2pm
  - wear long-sleeve shirts, pants, hats, and sunglasses
- children under 6 months: Ask a doctor

Inactive Ingredients

DI Water, Ethylhexyl Stearate/Ethylhexyl Palmitate/Diethylhexy Adipate, Propylene Glycol, Glyceryl Stearate (and) PEG-100 Stearate, Cetearyl Alcohol (and) Cetearth-20, Xanthan Gum, Imidazolidinyl Urea, Methyl Paraben, Propyl Paraben, Oleth 3 Phosphate, Vitamin E

Other Information

- protect this product from excessive heat and direct sun

Questions or Samples?

1-888-860-7424

Manufactured by:
R&R Lotion
15547 N. 77th Street
Scottsdale, AZ 85260

PRINCIPAL DISPLAY PANEL - 946 ml Bottle Label

SPF 36

BEACH CLUB
MINERAL SUNSCREEN

Broad Spectrum

32oz. (946ml) ℮